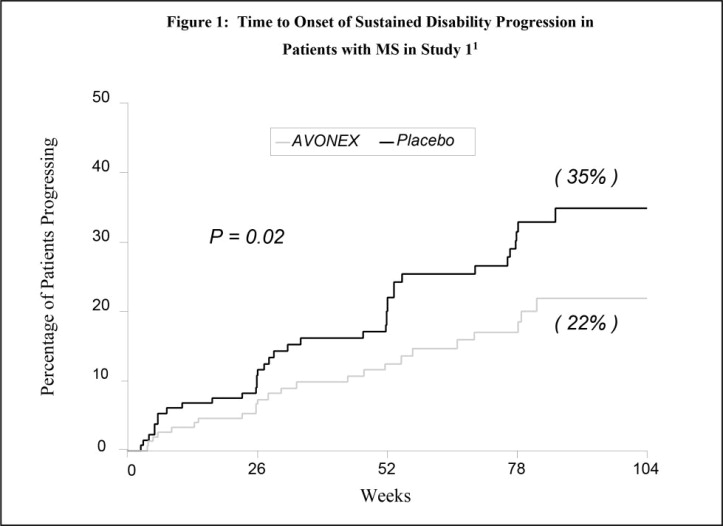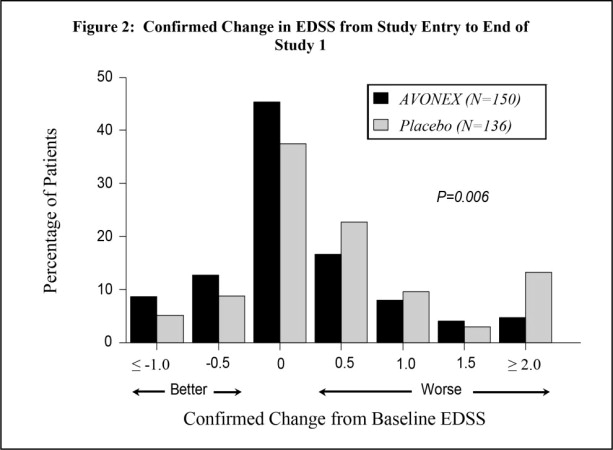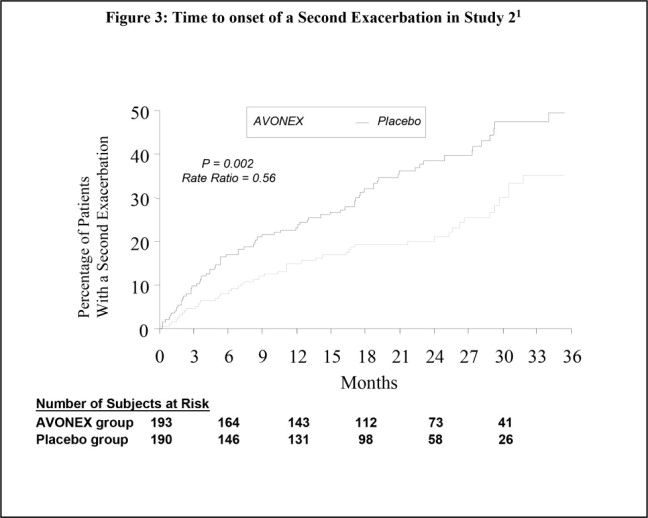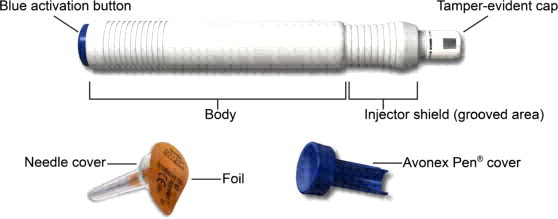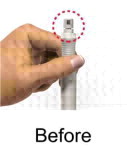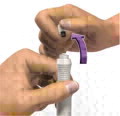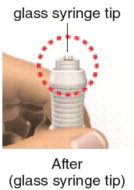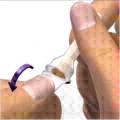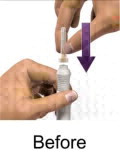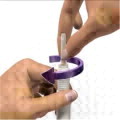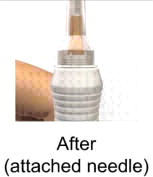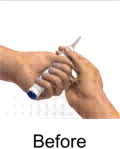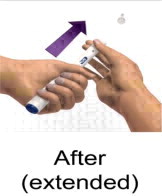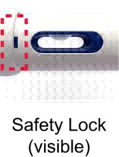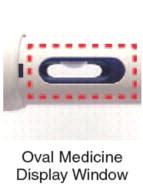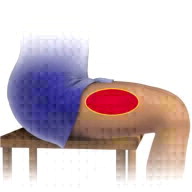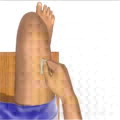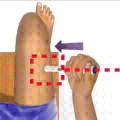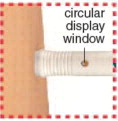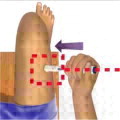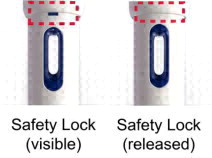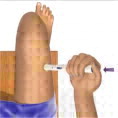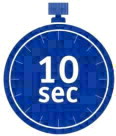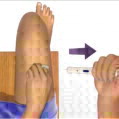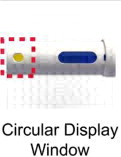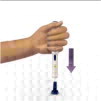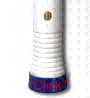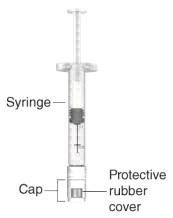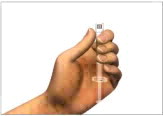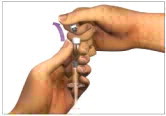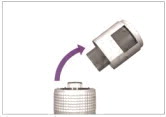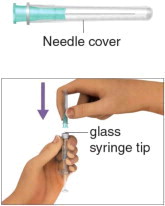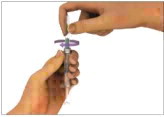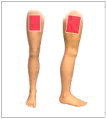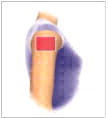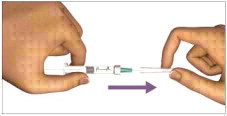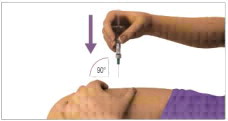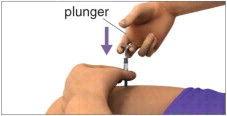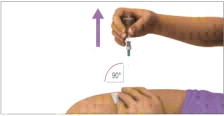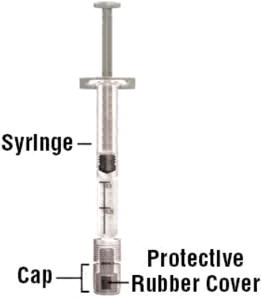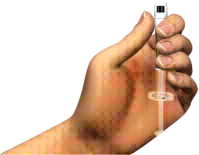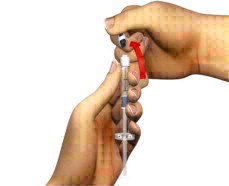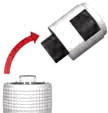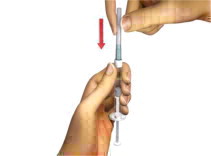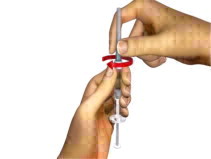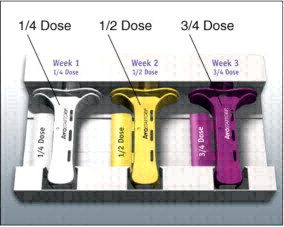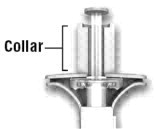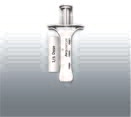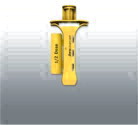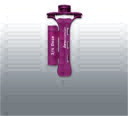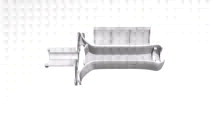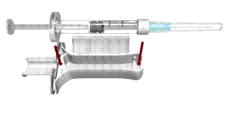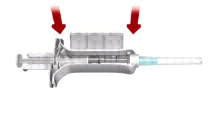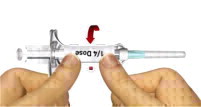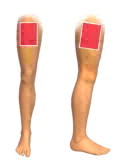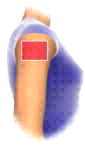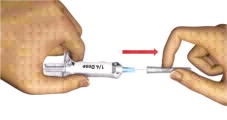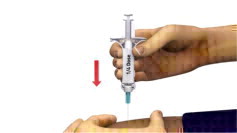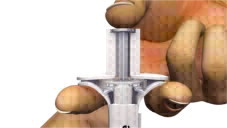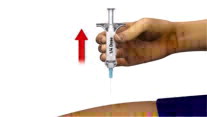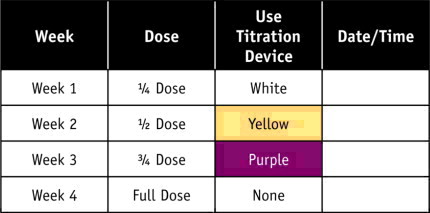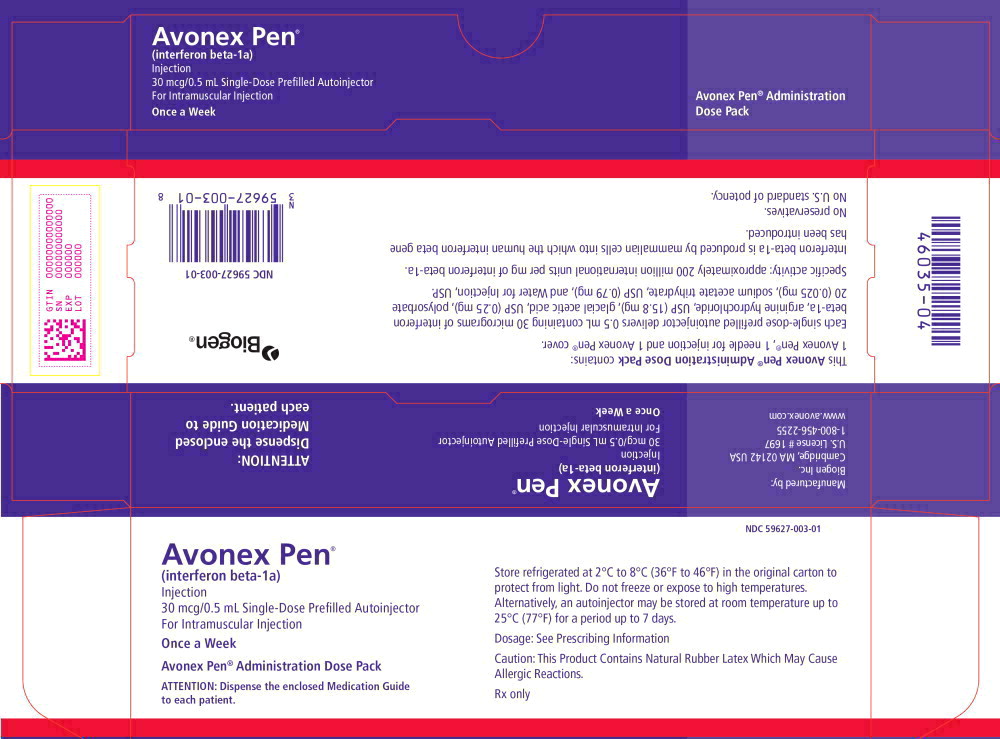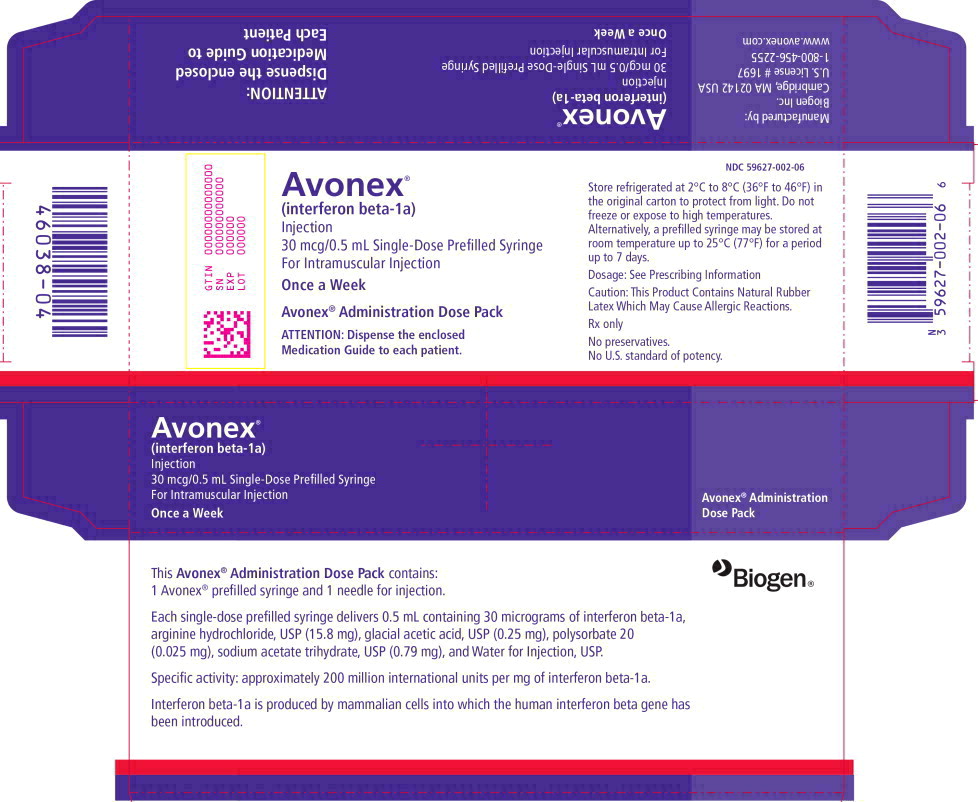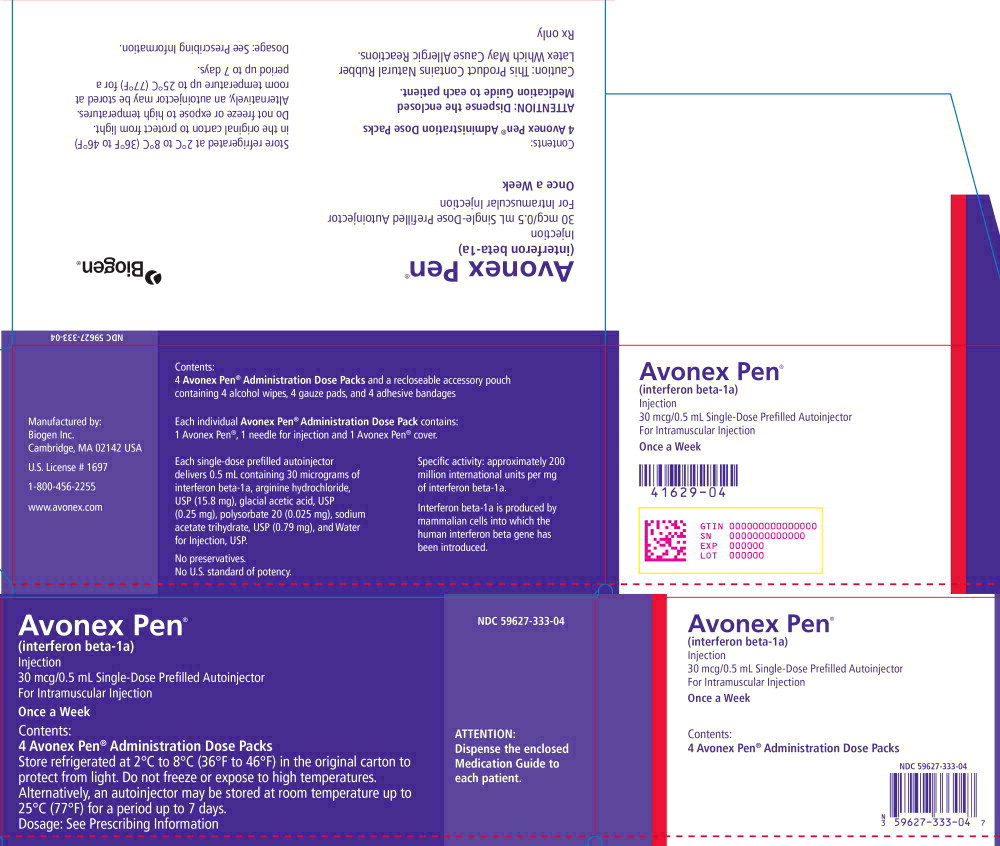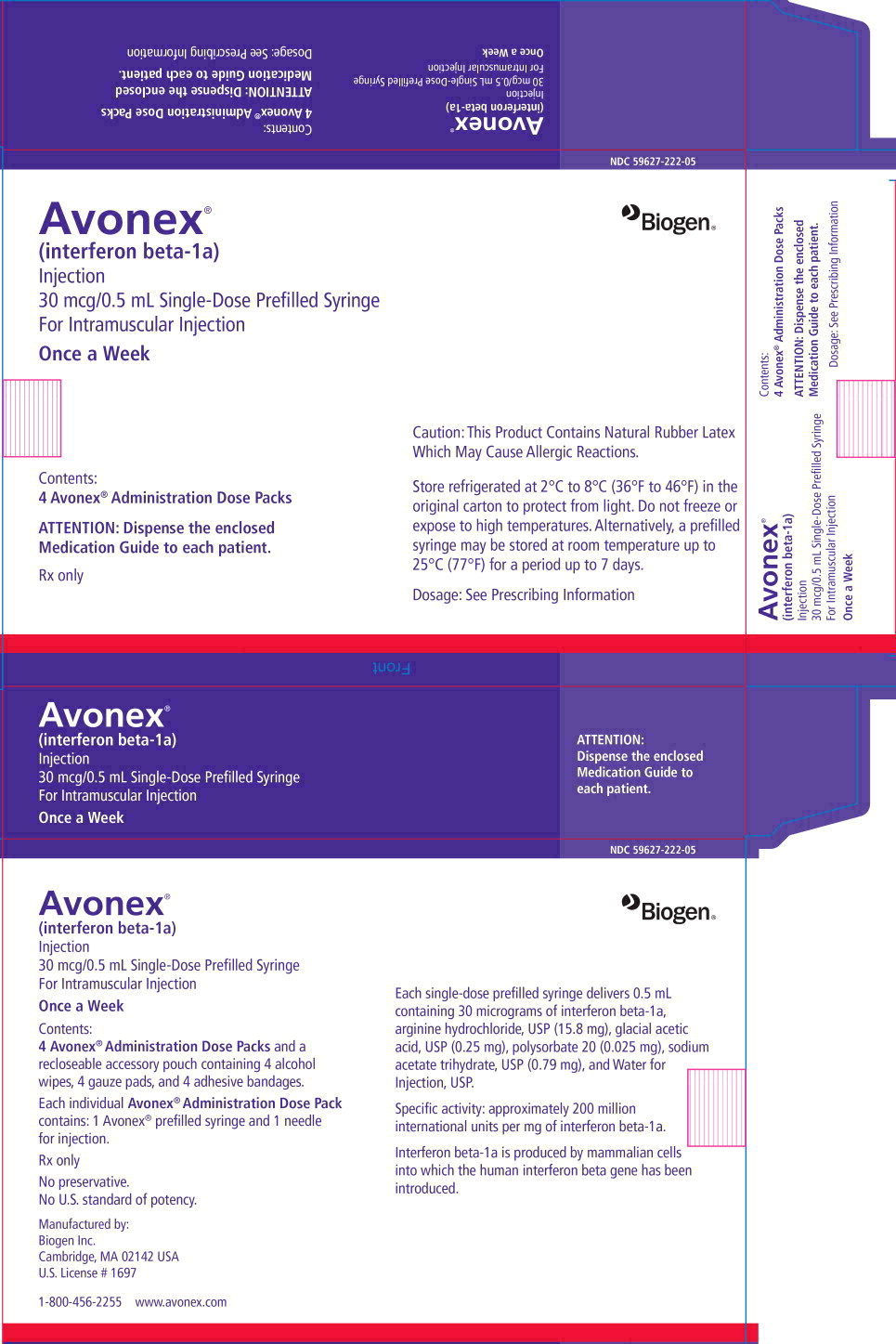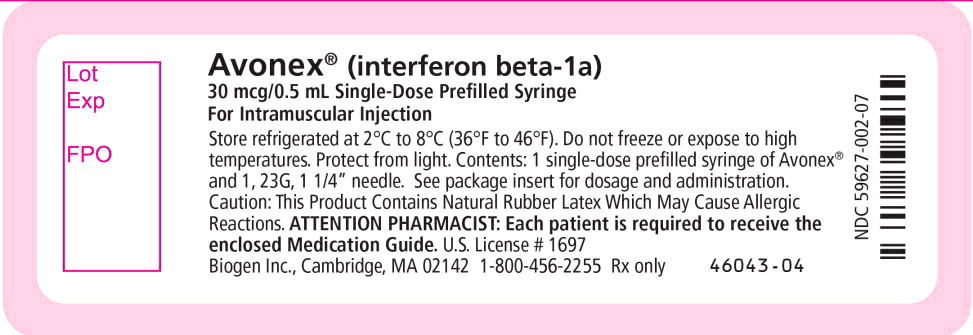 DRUG LABEL: AVONEX
NDC: 59627-333 | Form: KIT | Route: INTRAMUSCULAR
Manufacturer: Biogen Inc.
Category: prescription | Type: HUMAN PRESCRIPTION DRUG LABEL
Date: 20251119

ACTIVE INGREDIENTS: interferon beta-1a 30 ug/0.5 mL; ISOPROPYL ALCOHOL
 0.7 mL/1 mL
INACTIVE INGREDIENTS: Sodium acetate 0.79 mg/0.5 mL; Arginine hydrochloride 15.8 mg/0.5 mL; Acetic Acid 0.25 mg/0.5 mL; Polysorbate 20 0.025 mg/0.5 mL; Water; WATER

HIGHLIGHTS OF PRESCRIBING INFORMATION

These highlights do not include all the information needed to use AVONEX safely and effectively. See full prescribing information for AVONEX.
AVONEX (interferon beta-1a) injection, for intramuscular injection
Initial U.S. Approval: 1996

RECENT MAJOR CHANGES

Warnings and Precautions (5.8) | 7/2023

1 INDICATIONS AND USAGE

AVONEX is for the treatment of relapsing forms of multiple sclerosis (MS), to include clinically isolated syndrome, relapsing-remitting disease, and active secondary progressive disease, in adults. (1)

2 DOSAGE AND ADMINISTRATION

- For intramuscular use only (2.1)
- Recommended dose: 30 micrograms once a week (2.1)
- AVONEX may be titrated, starting with 7.5 micrograms for first week, to reduce flu-like symptoms (2.1)
- Increase dose by 7.5 micrograms each week for next 3 weeks until recommended dose of 30 micrograms (2.1)
- See patient instructions for use for complete administration instructions (2.2)
- Perform first injection under the supervision of an appropriately qualified health care professional (2.2)
- Analgesics and/or antipyretics on treatment days may help ameliorate flu-like symptoms (2.3)

3 DOSAGE FORMS AND STRENGTHS

- Injection: 30 micrograms per 0.5 mL solution in single-dose prefilled syringe (3)
- Injection: 30 micrograms per 0.5 mL solution in single-dose prefilled autoinjector (3)

4 CONTRAINDICATIONS

- History of hypersensitivity to natural or recombinant interferon beta, albumin or any other component of the formulation (4)

5 WARNINGS AND PRECAUTIONS

- Depression, Suicide, and Psychotic Disorders: advise patients to immediately report any symptoms of depression, suicidal ideation, and/or psychosis; consider discontinuation of AVONEX if depression occurs (5.1)
- Hepatic Injury: monitor liver function tests; monitor patients for signs and symptoms of hepatic injury; consider discontinuation of AVONEX if hepatic injury occurs (5.2, 5.10)
- Injection Site Reactions: Do not administer AVONEX into affected area until fully healed; if multiple lesions occur, change injection site or discontinue AVONEX until healing of skin lesions (5.4).
- Anaphylaxis and Other Allergic-Reactions: Discontinue if occurs (5.4)
- Congestive Heart Failure: monitor patients with pre-existing significant cardiac disease for worsening of cardiac symptoms (5.5)
- Decreased Peripheral Blood Counts: monitor complete blood count (5.6, 5.10)
- Thrombotic Microangiopathy: Cases of thrombotic microangiopathy have been reported. Discontinue AVONEX if clinical symptoms and laboratory findings consistent with TMA occur (5.7)
- Pulmonary Arterial Hypertension: Cases of pulmonary arterial hypertension (PAH) have been reported in patients treated with interferon beta products, including AVONEX. Discontinue AVONEX if PAH is diagnosed (5.8)
- Autoimmune Disorders: consider discontinuation of AVONEX if new autoimmune disorder occurs (5.10, 5.11)

6 ADVERSE REACTIONS

The most common adverse reactions (at least 5% more frequent on AVONEX than on placebo) were flu-like symptoms including chills, fever, myalgia, and asthenia. (6.1)

To report SUSPECTED ADVERSE REACTIONS, contact Biogen at 1-800-456-2255 or FDA at 1-800-FDA-1088 or www.fda.gov/medwatch.

8 USE IN SPECIFIC POPULATIONS

- Pregnancy: Epidemiological data do not suggest a clear relationship between interferon beta use and major congenital malformations, but interferon beta may cause fetal harm based on animal data. (8.1)

FULL PRESCRIBING INFORMATION

1 INDICATIONS AND USAGE

AVONEX is indicated for the treatment of relapsing forms of multiple sclerosis (MS), to include clinically isolated syndrome, relapsing-remitting disease, and active secondary progressive disease, in adults.

2 DOSAGE AND ADMINISTRATION

2.1 Dosing Information

AVONEX is administered intramuscularly.

The recommended dose is 30 micrograms once a week. To reduce the incidence and severity of flu-like symptoms that may occur when initiating AVONEX therapy at a dose of 30 micrograms, AVONEX may be started at a dose of 7.5 micrograms and the dose may be increased by 7.5 micrograms each week for the next three weeks until the recommended dose of 30 micrograms is achieved (see Table 1). An AVOSTARTGRIP™ kit containing 3 titration devices can be used for titration and is to be used only with AVONEX Prefilled Syringes.

Table 1: Schedule for Dose Titration
 | AVONEX Dose^1 | Recommended Dose
Week 1 | 7.5 micrograms | 1/4 dose
Week 2 | 15 micrograms | 1/2 dose
Week 3 | 22.5 micrograms | 3/4 dose
Week 4+ | 30 micrograms | full dose
^1 Dosed once a week, intramuscularly

2.2 Important Administration Instructions (All Dosage Forms)

AVONEX dosage forms (prefilled syringe and prefilled autoinjector) are single-dose. See Patient's Instructions for Use for complete administration instructions.

The first AVONEX injection should be performed under the supervision of an appropriately qualified healthcare professional. If patients or caregivers are to administer AVONEX, train them in the proper intramuscular injection technique and assess their ability to inject intramuscularly to ensure the proper administration of AVONEX.

Advise patients and caregivers to:

- Rotate injection sites with each administration to minimize the likelihood of injection site reactions, including necrosis or localized infection [see Warnings and Precautions (5.4)]
- NOT inject into an area of the body where the skin is irritated, reddened, bruised, infected or scarred in any way
- Check the injection site after 2 hours for redness, swelling, or tenderness
- Contact their healthcare provider if they have a skin reaction and it does not clear up in a few days

Parenteral drug products should be inspected visually for particulate matter and discoloration prior to administration, whenever solution and container permit.

A 25 gauge, 1” needle for intramuscular injection with AVONEX prefilled syringe may be substituted for the 23 gauge, 1 ¼” needle by the healthcare provider, if deemed appropriate. A 25 gauge, 5/8” needle specific to the prefilled autoinjector is supplied with the AVONEX PEN® Administration Dose Pack. DO NOT use any other needle with the autoinjector.

Use safe disposal procedures for needles and syringes. DO NOT re-use needles, prefilled syringes, or autoinjectors. Following the administration of each titrated dose, discard any remaining product.

2.3 Premedication for Flu-like Symptoms

Concurrent use of analgesics and/or antipyretics on treatment days may help ameliorate flu-like symptoms associated with AVONEX use.

3 DOSAGE FORMS AND STRENGTHS

- Injection: 30 micrograms per 0.5 mL clear, colorless solution in a single-dose prefilled syringe
- Injection: 30 micrograms per 0.5 mL clear, colorless solution in a single-dose prefilled autoinjector

4 CONTRAINDICATIONS

AVONEX is contraindicated in patients with a history of hypersensitivity to natural or recombinant interferon beta, or any other component of the formulation [see Warnings and Precautions (5.3)].

The formerly available lyophilized vial formulation of AVONEX is contraindicated in patients with a history of hypersensitivity to albumin (human).

5 WARNINGS AND PRECAUTIONS

5.1 Depression, Suicide, and Psychotic Disorders

Patients treated with AVONEX and their caregivers should be advised to report immediately any symptoms of depression, suicidal ideation, and/or psychosis to their prescribing physicians. If a patient develops depression or other severe psychiatric symptoms, cessation of AVONEX therapy should be considered.

Depression and suicide have been reported to occur with increased frequency in patients receiving AVONEX. In Study 1, the incidence of depression was similar in placebo-treated and in AVONEX-treated patients, but suicidal tendency was seen more frequently in AVONEX-treated patients (4% in AVONEX group vs. 1% in placebo group). In Study 2, there was a greater incidence of depression in AVONEX-treated patients than in placebo-treated patients (20% in AVONEX group vs. 13% in placebo group) [see Clinical Studies (14)].

Additionally, there have been postmarketing reports of depression, suicidal ideation, and/or development of new or worsening of other pre-existing psychiatric disorders, including psychosis. For some of these patients, symptoms of depression improved upon cessation of AVONEX.

5.2 Hepatic Injury

Severe hepatic injury, including cases of hepatic failure, has been reported rarely in patients taking AVONEX. Asymptomatic elevation of hepatic transaminases has also been reported, and in some patients has recurred upon rechallenge with AVONEX. In some cases, these events have occurred in the presence of other drugs that have been associated with hepatic injury. The potential risk of AVONEX used in combination with known hepatotoxic drugs or other products (e.g., alcohol) should be considered prior to starting AVONEX, or before starting hepatotoxic drugs. Patients should be monitored for signs of hepatic injury [see Warnings and Precautions (5.10)].

5.3 Anaphylaxis and Other Allergic-Reactions

Anaphylaxis has been reported as a rare complication of AVONEX use. Other allergic reactions have included dyspnea, orolingual edema, skin rash and urticaria. Discontinue AVONEX if anaphylaxis or other allergic reactions occur.

5.4 Injection Site Reactions Including Necrosis

Injection site reactions, including injection site necrosis, can occur with the use of interferon beta products, including AVONEX. In controlled clinical trials, injection site reactions (e.g., injection site pain, bruising or erythema) occurred in 18% of patients receiving AVONEX and 13% in the placebo group. These reactions included injection site inflammation (6%), injection site pain (8%), injection site mass (<1%), nonspecific reactions.

Injection site abscesses and cellulitis and injection site necrosis have been reported in the postmarketing setting with interferon beta products, including AVONEX. Some cases required treatment with hospitalization for surgical drainage and intravenous antibiotics.

Periodically evaluate patient understanding and use of aseptic self-injection techniques and procedures, particularly if injection site necrosis has occurred. Whether to discontinue therapy following a single site of necrosis is dependent on the extent of necrosis. For patients who continue therapy with AVONEX after injection site necrosis has occurred, avoid administration of AVONEX into the affected area until it is fully healed. If multiple lesions occur, change injection site or discontinue therapy until healing occurs.

5.5 Congestive Heart Failure

Patients with pre-existing congestive heart failure should be monitored for worsening of their cardiac condition during initiation of and continued treatment with AVONEX. While beta interferons do not have any known direct cardiac toxicity, during the postmarketing period cases of congestive heart failure, cardiomyopathy, and cardiomyopathy with congestive heart failure have been reported in patients without known predisposition to these events, and without other etiologies being established. In some cases, these events have been temporally related to the administration of AVONEX. In some of these instances recurrence upon rechallenge was observed.

5.6 Decreased Peripheral Blood Counts

Decreased peripheral blood counts in all cell lines, including rare pancytopenia and thrombocytopenia, have been reported from postmarketing experience in AVONEX-treated patients [see Adverse Reactions (6.2)]. In some cases, platelet counts were below 10,000/microliter. Some cases recurred with rechallenge [see Adverse Reactions (6.2)]. Patients should be monitored for symptoms or signs of decreased blood counts.

5.7 Thrombotic Microangiopathy

Cases of thrombotic microangiopathy (TMA), including thrombotic thrombocytopenic purpura and hemolytic uremic syndrome, some fatal, have been reported with interferon beta products, including AVONEX. Cases have been reported several weeks to years after starting interferon beta products. Discontinue AVONEX if clinical symptoms and laboratory findings consistent with TMA occur, and manage as clinically indicated.

5.8 Pulmonary Arterial Hypertension

Cases of pulmonary arterial hypertension (PAH) have been reported in patients treated with interferon beta products, including AVONEX. PAH has occurred in patients treated with interferon beta products in the absence of other contributory factors. Many of the reported cases required hospitalization, including one case with interferon beta in which the patient underwent a lung transplant. PAH has developed at various time points after initiating therapy with interferon beta products and may occur several years after starting treatment.

Patients who develop unexplained symptoms (e.g., dyspnea, new or increasing fatigue) should be assessed for PAH. If alternative etiologies have been ruled out and a diagnosis of PAH is confirmed, discontinue treatment and manage as clinically indicated.

5.9 Seizures

Seizures have been temporally associated with the use of beta interferons in clinical trials and postmarketing safety surveillance. In the two placebo-controlled studies in multiple sclerosis (Studies 1 and 2), 4 patients receiving AVONEX experienced seizures, while no seizures occurred in the placebo group [see Clinical Studies (14)]. Three of these 4 patients had no prior history of seizure [see Adverse Reactions (6.1)]. It is not known whether these events were related to the effects of multiple sclerosis alone, to AVONEX, or to a combination of both.

5.10 Autoimmune Disorders

Postmarketing reports of autoimmune disorders of multiple target organs in AVONEX-treated patients included idiopathic thrombocytopenia, hyper- and hypothyroidism, and rare cases of autoimmune hepatitis. If AVONEX-treated patients develop a new autoimmune disorder, consider stopping the therapy.

5.11 Laboratory Tests

In addition to those laboratory tests normally required for monitoring patients with multiple sclerosis, complete blood and differential white blood cell counts, platelet counts, and blood chemistries, including liver function tests, are recommended during AVONEX therapy [see Warnings and Precautions (5.2, 5.6, 5.10)]. Patients with myelosuppression may require more intensive monitoring of complete blood cell counts, with differential and platelet counts. Thyroid function should be monitored periodically. If patients have or develop symptoms of thyroid dysfunction (hypo- or hyperthyroidism), thyroid function tests should be performed according to standard medical practice.

6 ADVERSE REACTIONS

The following serious adverse reactions are discussed in more detail in other sections of labeling:

- Depression, Suicide, and Psychotic Disorders [see Warnings and Precautions (5.1)]
- Hepatic Injury [see Warnings and Precautions (5.2)]
- Anaphylaxis and Other Allergic-Reactions [see Warnings and Precautions (5.3)]
- Injection Site Reactions Including Necrosis [see Warnings and Precautions (5.4)]
- Congestive Heart Failure [see Warnings and Precautions (5.5)]
- Decreased Peripheral Blood Counts [see Warnings and Precautions (5.6)]
- Thrombotic Microangiopathy [see Warnings and Precautions (5.7)]
- Pulmonary Arterial Hypertension [see Warnings and Precautions (5.8)]
- Seizures [see Warnings and Precautions (5.9)]
- Autoimmune Disorders [see Warnings and Precautions (5.10)]
- Laboratory Tests [see Warnings and Precautions (5.11)]

6.1 Clinical Trials Experience

Because clinical trials are conducted under widely varying conditions, adverse reaction rates observed in the clinical trials of AVONEX cannot be directly compared to rates in clinical trials of other drugs and may not reflect the rates observed in practice.

Among 351 patients with relapsing forms of MS treated with AVONEX 30 micrograms (including 319 patients treated for 6 months and 288 patients treated for greater than one year) the most commonly reported adverse reactions (at least 5% more frequent on AVONEX than on placebo) were flu-like symptoms. Symptoms can include chills, fever, myalgia and asthenia occurring within hours to days following an injection. Most people who take AVONEX have flu-like symptoms early during the course of therapy. Usually, these symptoms last for a day after the injection. For many people, these symptoms lessen or go away over time. The most frequently reported adverse reactions resulting in clinical intervention (for example, discontinuation of AVONEX or the need for concomitant medication to treat an adverse reaction symptom) were flu-like symptoms and depression.

Table 2 enumerates adverse reactions that occurred with AVONEX-treated patients at an incidence of at least 2% more than that observed in the placebo-treated patients in the pooled placebo-controlled studies in patients with relapsing forms of MS [see Clinical Studies (14)].

Table 2: Adverse Reactions in the Placebo-Controlled Studies
 | Placebo | AVONEX
Adverse Reaction | (N = 333) | (N = 351)
Body as a Whole
Headache | 55% | 58%
Flu-like symptoms (otherwise unspecified) | 29% | 49%
Pain | 21% | 23%
Asthenia | 18% | 24%
Fever | 9% | 20%
Chills | 5% | 19%
Abdominal pain | 6% | 8%
Injection site pain | 6% | 8%
Infection | 4% | 7%
Injection site inflammation | 2% | 6%
Chest pain | 2% | 5%
Injection site reaction | 1% | 3%
Toothache | 1% | 3%
Nervous System
Depression | 14% | 18%
Dizziness | 12% | 14%
Respiratory System
Upper respiratory tract infection | 12% | 14%
Sinusitis | 12% | 14%
Bronchitis | 5% | 8%
Digestive System
Nausea | 19% | 23%
Musculoskeletal System
Myalgia | 22% | 29%
Arthralgia | 6% | 9%
Urogenital
Urinary tract infection | 15% | 17%
Urine constituents abnormal | 0% | 3%
Skin and Appendages
Alopecia | 2% | 4%
Special Senses
Eye disorder | 2% | 4%
Hemic and Lymphatic System
Injection site ecchymosis | 4% | 6%
Anemia | 1% | 4%
Cardiovascular System
Migraine | 3% | 5%
Vasodilation | 0% | 2%

Immunogenicity

Anaphylaxis and other allergic reactions have occurred in AVONEX-treated patients [see Warnings and Precautions (5.3)]. As with all therapeutic proteins, there is a potential for immunogenicity. In studies assessing immunogenicity in multiple sclerosis patients administered AVONEX for at least 1 year, 5% (21 of 390 patients) showed the presence of neutralizing antibodies at one or more times.

These data reflect the percentage of patients whose test results were considered positive for antibodies to AVONEX using a two-tiered assay (ELISA binding assay followed by an antiviral cytopathic effect assay), and are highly dependent on the sensitivity and specificity of the assay. Additionally, the observed incidence of neutralizing activity in an assay may be influenced by several factors including sample handling, timing of sample collection, concomitant medications, and underlying disease. For these reasons, comparison of the incidence of antibodies to AVONEX with the incidence of antibodies to other products may be misleading.

6.2 Postmarketing Experience

The following additional adverse reactions have been identified during post-approval use of AVONEX. Because these reactions are reported voluntarily from a population of uncertain size, it is not always possible to reliably estimate their frequency or establish a causal relationship to drug exposure.

- Hemolytic anemia
- Menorrhagia and metrorrhagia
- Pulmonary Arterial Hypertension
- Rash (including vesicular rash)
- Rare cases of injection site abscess or cellulitis requiring surgical intervention

8 USE IN SPECIFIC POPULATIONS

8.1 Pregnancy

Risk Summary

Data from a large population-based cohort study, as well as other published studies over several decades, have not identified a drug-associated risk of major birth defects with the use of interferon beta products during early pregnancy. Findings regarding a potential risk for low birth weight or miscarriage with the use of interferon beta products in pregnancy have been inconsistent (see Data). In a study in pregnant monkeys, administration of interferon beta during pregnancy resulted in an increased rate of abortion at doses greater than those used clinically (see Data).

In the U.S. general population, the estimated background risk of major birth defects and miscarriage in clinically recognized pregnancies is 2% to 4% and 15% to 20%, respectively. The background risk of major birth defects and miscarriage for the indicated population is unknown.

Data

Human Data

The majority of observational studies reporting on pregnancies exposed to interferon beta products did not identify an association between the use of interferon beta products during early pregnancy and an increased risk of major birth defects.

In a population-based cohort study conducted in Finland and Sweden, data were collected from 1996--2014 in Finland and 2005--2014 in Sweden on 2,831 pregnancy outcomes from women with MS. 797 pregnancies were in women exposed to interferon beta only. No evidence was found of an increased risk of major birth defects among women with MS exposed to interferon beta products compared to women with MS that were unexposed to any non-steroid therapy for MS (n=1,647) within the study. No increased risks were observed for miscarriages and ectopic pregnancies, though there were limitations in obtaining complete data capture for these outcomes, making the interpretation of the findings more difficult.

Two small cohort studies that examined pregnancies exposed to interferon beta products (without differentiating between subtypes of interferon beta products) suggested that a decrease in mean birth weight may be associated with interferon beta exposure during pregnancy, but this finding was not confirmed in larger observational studies. Two small studies observed an increased prevalence of miscarriage, although the finding was only statistically significant in one study. Most studies enrolled patients later in pregnancy which made it difficult to ascertain the true percentage of miscarriages. In one small cohort study, a significantly increased risk of preterm birth following interferon beta exposure during pregnancy was observed.

Animal Data

In pregnant monkeys given interferon beta at 100 times the recommended weekly human dose (based upon a body surface area [mg/m^2] comparison), no adverse effects on embryofetal development were observed. Abortifacient activity was evident following 3 to 5 doses at this level. No abortifacient effects were observed in monkeys treated at 2 times the recommended weekly human dose (based upon mg/m^2).

8.2 Lactation

Risk Summary

Limited published literature has described the presence of interferon beta-1a products in human milk at low levels. There are no data on the effects of interferon beta-1a on milk production. Therefore, the developmental and health benefits of breastfeeding should be considered along with the mother's clinical need for AVONEX and any potential adverse effects on the breastfed infant from AVONEX or from the underlying maternal condition.

8.4 Pediatric Use

Safety and effectiveness in pediatric patients have not been established.

8.5 Geriatric Use

Clinical studies of AVONEX did not include sufficient numbers of patients aged 65 and over to determine whether they respond differently than younger patients.

11 DESCRIPTION

Interferon beta-1a, an interferon beta, is a 166 amino acid glycoprotein with a molecular weight of approximately 22,500 daltons. It is produced by recombinant DNA technology using genetically engineered Chinese Hamster Ovary cells into which the human interferon beta gene has been introduced. The amino acid sequence of AVONEX is identical to that of natural human interferon beta.

Using the World Health Organization (WHO) International Standard for Interferon, AVONEX has a specific activity of approximately 200 million international units of antiviral activity per mg of interferon beta-1a determined specifically by an in vitro cytopathic effect bioassay using lung carcinoma cells (A549) and Encephalomyocarditis virus (ECM). AVONEX 30 micrograms contains approximately 6 million international units of antiviral activity using this method. The activity against other standards is not known. Comparison of the activity of AVONEX with other interferon betas is not appropriate, because of differences in the reference standards and assays used to measure activity.

AVONEX (interferon beta-1a) injection is a sterile liquid for intramuscular injection available in a prefilled glass syringe or a prefilled glass syringe surrounded by an autoinjector. Each single-dose prefilled glass syringe or single-dose prefilled autoinjector delivers 0.5 mL of solution containing 30 micrograms of interferon beta-1a, arginine hydrochloride, USP (15.8 mg), glacial acetic acid, USP (0.25 mg), polysorbate 20 (0.025 mg), sodium acetate trihydrate, USP (0.79 mg), and Water for Injection, USP at a pH of approximately 4.8.

12 CLINICAL PHARMACOLOGY

12.1 Mechanism of Action

The mechanism of action by which AVONEX exerts its effects in patients with multiple sclerosis is unknown.

12.2 Pharmacodynamics

Interferons (IFNs) are a family of naturally occurring proteins, produced by eukaryotic cells in response to viral infection and other biologic agents. Three major types of interferons have been defined: type I (IFN-alpha, beta, epsilon, kappa and omega), type II (IFN–gamma) and type III (IFN-lambda). Interferon-beta is a member of the type I subset of interferons. The type I interferons have considerably overlapping but also distinct biologic activities. The bioactivities of all IFNs, including IFN-beta, are induced via their binding to specific receptors on the membranes of human cells. Differences in the bioactivities induced by the three major subtypes of IFNs likely reflect differences in the signal transduction pathways induced by signaling through their cognate receptors.

Interferon beta exerts its biological effects by binding to specific receptors on the surface of human cells. This binding initiates a complex cascade of intracellular events that leads to the expression of numerous interferon-induced gene products and markers. These include 2', 5'-oligoadenylate synthetase, β2-microglobulin, and neopterin. These products have been measured in the serum and cellular fractions of blood collected from patients treated with AVONEX.

Clinical studies conducted in multiple sclerosis patients showed that interleukin 10 (IL-10) levels in cerebrospinal fluid were increased in patients treated with AVONEX compared to placebo. Serum IL-10 levels maximally were increased by 48 hours after intramuscular injection of AVONEX and remained elevated for 1 week. However, no relationship has been established between absolute levels of IL-10 and clinical outcome in multiple sclerosis.

12.3 Pharmacokinetics

Pharmacokinetics of AVONEX in multiple sclerosis patients have not been evaluated. The pharmacokinetic and pharmacodynamic profiles of AVONEX in healthy subjects following doses of 30 micrograms through 75 micrograms have been investigated. Serum levels of AVONEX as measured by antiviral activity are slightly above detectable limits following a 30 microgram intramuscular dose, and increase with higher doses.

After an intramuscular dose, serum levels of AVONEX generally peak at 15 hours post-dose (range: 6-36 hours) and then decline at a rate consistent with a 19 (range: 8-54) hour elimination half-life.

Subcutaneous administration of AVONEX should not be substituted for intramuscular administration as there is no data establishing that subcutaneous and intramuscular administration of AVONEX result in equivalent pharmacokinetic and pharmacodynamic parameters.

Biological response markers (e.g., neopterin and β2-microglobulin) are induced by AVONEX following parenteral doses of 15 micrograms through 75 micrograms in healthy subjects and treated patients. Biological response marker levels increase within 12 hours of dosing and remain elevated for at least 4 days. Peak biological response marker levels are typically observed 48 hours after dosing. The relationship of serum AVONEX levels or levels of these induced biological response markers to the mechanisms by which AVONEX exerts its effects in multiple sclerosis is unknown.

13 NONCLINICAL TOXICOLOGY

13.1 Carcinogenesis, Mutagenesis, and Impairment of Fertility

Carcinogenesis: The carcinogenic potential of AVONEX has not been tested in animals.

Mutagenesis: Interferon beta was not mutagenic when tested in an in vitro bacterial reverse mutation (Ames) test or in an in vitro cytogenetic assay in human lymphocytes.

Impairment of Fertility: In monkeys administered interferon beta by subcutaneous injection (8 to 15 doses of 1.25 mcg/kg or 50 mcg/kg) over the course of one menstrual cycle, menstrual irregularities, anovulation, and decreased serum progesterone levels were observed at the higher dose. These effects were reversible after discontinuation of drug. The no-effect dose (1.25 mcg/kg) is approximately 2 times the recommended weekly dose in humans (30 mcg) on a mg/m^2 basis.

14 CLINICAL STUDIES

The clinical effects of AVONEX in patients with relapsing forms of multiple sclerosis (MS) were studied in two randomized, multicenter, double-blind, placebo-controlled studies in patients with MS (Studies 1 and 2). Safety and efficacy of treatment with AVONEX beyond 3 years is not known.

In Study 1, 301 patients received either 30 micrograms of AVONEX (n=158) or placebo (n=143) by intramuscular injection once weekly. Patients received injections for up to 2 years, and continued to be followed until study completion. Two hundred eighty-two patients completed 1 year on study, and 172 patients completed 2 years on study. There were 144 patients treated with AVONEX for more than 1 year, 115 patients for more than 18 months and 82 patients for 2 years.

All patients had a definite diagnosis of multiple sclerosis of at least 1 year duration and had at least 2 exacerbations in the 3 years prior to study entry (or 1 per year if the duration of disease was less than 3 years). At entry, study participants were without exacerbation during the prior 2 months and had Kurtzke Expanded Disability Status Scale (EDSS^3) scores ranging from 1.0 to 3.5. The EDSS is a scale that quantifies disability in patients with MS and ranges from 0 (normal neurologic exam) to 10 (death due to MS). Patients with chronic progressive multiple sclerosis were excluded from this study.

Disability

The primary outcome assessment was time to progression in disability, measured as an increase in the EDSS score of at least 1 point that was sustained for at least 6 months. An increase in EDSS score reflects accumulation of disability. This endpoint was used to help distinguish permanent increase in disability from a transient increase due to an exacerbation.

As shown in Figure 1, the time to onset of sustained progression in disability was significantly longer in AVONEX-treated patients than in placebo-treated patients in Study 1 (p = 0.02). The percentage of patients progressing by the end of 2 years was 35% for placebo-treated patients and 22% for AVONEX-treated patients. This represents a 37% relative reduction in the risk of accumulating disability in the AVONEX-treated group compared to the placebo-treated group.

^1Kaplan-Meier Methodology; Disability progression was defined as at least a 1 point increase in EDSS score sustained for at least 6 months.

The distribution of confirmed EDSS change from study entry (baseline) to the end of the study is shown in Figure 2. There was a statistically significant difference between the AVONEX and placebo groups in confirmed change for patients with at least 2 scheduled visits (p = 0.006).

Exacerbations

The rate and frequency of MS exacerbations were secondary outcomes. For all patients included in the study, irrespective of time on study, the annual exacerbation rate was 0.67 per year in the AVONEX-treated group and 0.82 per year in the placebo-treated group (p = 0.04).

AVONEX treatment significantly decreased the frequency of exacerbations in the subset of patients who were enrolled in the study for at least 2 years (87 placebo-treated patients and 85 AVONEX-treated patients; p = 0.03; see Table 3).

MRI Results

Gadolinium (Gd)-enhanced and T2-weighted magnetic resonance imaging (MRI) scans of the brain were obtained in most patients at baseline and at the end of 1 and 2 years of treatment. Secondary outcomes included Gd-enhanced lesion number and volume, and T2-weighted lesion volume. Gd-enhancing lesions seen on brain MRI scans represent areas of breakdown of the blood brain barrier thought to be secondary to inflammation. AVONEX-treated patients demonstrated significantly lower Gd-enhanced lesion number after 1 and 2 years of treatment than placebo-treated patients (p ≤ 0.05; see Table 3). The volume of Gd-enhanced lesions showed similar treatment effects in the AVONEX and placebo groups (p ≤ 0.03). Percentage change in T2-weighted lesion volume from study entry to Year 1 was significantly lower in AVONEX-treated than placebo-treated patients (p = 0.02). A significant difference in T2-weighted lesion volume change was not seen between study entry and Year 2 in the AVONEX and placebo groups.

Summary of Effects of Clinical and MRI Endpoints in Study 1

A summary of the effects of AVONEX on the clinical and MRI endpoints of this study is presented in Table 3.

Table 3: Clinical and MRI Endpoints in Patients with MS in Study 1
Endpoint | Placebo | AVONEX | P-Value
PRIMARY ENDPOINT:
Time to sustained progression in disability (N: 143, 158)^1 | --- See Figure 1 --- |  | 0.02^2
Percentage of patients progressing in disability at 2 years (Kaplan-Meier estimate)^1 | 35% | 22%
SECONDARY ENDPOINTS: DISABILITY
Mean confirmed change in EDSS from study entry to end of study (N: 136, 150)^1 | 0.50 | 0.20 | 0.006^3
EXACERBATIONS
Number of exacerbations in subset completing 2 years (N: 87, 85)
0 | 26% | 38% | 0.03^3
1 | 30% | 31%
2 | 11% | 18%
3 | 14% | 7%
≥ 4 | 18% | 7%
Percentage of patients exacerbation-free in subset completing 2 years (N: 87, 85) | 26% | 38% | 0.10^4
Annual exacerbation rate (N: 143, 158)1 | 0.82 | 0.67 | 0.04^5

Table 3 (continued): Clinical and MRI Endpoints in Study 1
Endpoint | Placebo | AVONEX | P-Value
MRI
Number of Gd-enhanced lesions:
At study entry (N: 132, 141)
Mean (Median) | 2.3 (1.0) | 3.2 (1.0)
Range | 0-23 | 0-56
Year 1 (N: 123, 134)
Mean (Median) | 1.6 (0) | 1.0 (0) | 0.02^3
Range | 0-22 | 0-28
Year 2 (N: 82, 83)
Mean (Median) | 1.6 (0) | 0.8 (0) | 0.05^3
Range | 0-34 | 0-13
T2 lesion volume:
Percentage change from study entry to Year 1 (N: 116, 123)
Median | -3.3% | -13.1% | 0.02^3
Percentage change from study entry to Year 2 (N: 83, 81)
Median | -6.5% | -13.2% | 0.36^3
Note: (N: ,) denotes the number of evaluable placebo and AVONEX patients, respectively.
^1 Patient data included in this analysis represent variable periods of time on study.
^2 Analyzed by Mantel-Cox (logrank) test.
^3 Analyzed by Mann-Whitney rank-sum test.
^4 Analyzed by Cochran-Mantel-Haenszel test.
^5 Analyzed by likelihood ratio test.

In Study 2, 383 patients who had recently experienced an isolated demyelinating event involving the optic nerve, spinal cord, or brainstem/cerebellum, and who had lesions typical of multiple sclerosis on brain MRI, received either 30 micrograms of AVONEX (n = 193) or placebo (n = 190) by intramuscular injection once weekly. Patients were enrolled into the study over a two-year period and followed for up to three years or until they developed a second clinical exacerbation in an anatomically distinct region of the central nervous system.

Exacerbations

In Study 2, the primary outcome measure was time to development of a second exacerbation in an anatomically distinct region of the central nervous system. Time to development of a second exacerbation was significantly delayed in AVONEX-treated compared to placebo-treated patients (p = 0.002). The Kaplan-Meier estimates of the percentage of patients developing an exacerbation within 24 months were 39% in the placebo group and 21% in the AVONEX group (see Figure 3). The relative rate of developing a second exacerbation in the AVONEX group was 0.56 of the rate in the placebo group (95% confidence interval 0.38 to 0.81).

^1 Kaplan-Meier Methodology

MRI Findings

Secondary outcomes were brain MRI measures, including the cumulative increase in the number of new or enlarging T2 lesions, T2 lesion volume at baseline compared to results at 18 months, and the number of Gd-enhancing lesions at 6 months. See Table 4 for the MRI results.

Table 4: Brain MRI Results in Study 2
 | AVONEX | Placebo
CHANGE FROM BASELINE IN T2 VOLUME OF LESIONS AT 18 MONTHS: | N = 119 | N = 109
Actual Change (mm^3)1* Median (25th%, 75th%) | 28 (-576, 397) | 313 (5, 1140)
Percentage Change1* Median (25th%, 75th%) | 1 (-24, 29) | 16 (0, 53)
NUMBER OF NEW OR ENLARGING T2 LESIONS AT 18 MONTHS 1*: | N = 132 N (%) |  | N = 119 N (%)
0 | 62 (47) | 22 (18)
1-3 | 41 (31) | 47 (40)
≥4 | 29 (22) | 50 (42)
Mean (SD) | 2.13 (3.2) | 4.97 (7.7)
NUMBER OF GD-ENHANCING LESIONS AT 6 MONTHS 2*: | N = 165 N (%) |  | N = 152 N (%)
0 | 115 (70) | 93 (61)
1 | 27 (16) | 16 (11)
>1 | 23 (14) | 43 (28)
Mean (SD) | 0.87 (2.3) | 1.49 (3.1)
^1 P value <0.001
^2 P value <0.03
* P value from a Mann-Whitney rank-sum test

16 HOW SUPPLIED/STORAGE AND HANDLING

16.1 How Supplied

AVONEX (interferon beta-1a) injection is a clear, colorless solution in a single-dose prefilled glass syringe or a single-dose prefilled autoinjector for intramuscular injection available in the following packaging configurations:

NDC number | Contents
NDC 59627-002-06 | one single-dose prefilled AVONEX syringe one 23-gauge, 1¼-inch needle
NDC 59627-222-05 | four single-dose prefilled AVONEX syringes four 23-gauge, 1¼-inch needles four alcohol wipes four gauze pads four adhesive bandages
NDC 59627-003-01 | one single-dose prefilled autoinjector (AVONEX Pen) one 25-gauge, 5/8-inch needle one AVONEX Pen cover
NDC 59627-333-04 | four single-dose prefilled autoinjector (AVONEX Pens) four 25-gauge, 5/8-inch needles four AVONEX Pen covers four alcohol wipes four gauze pads four adhesive bandages

16.2 Storage and Handling

Refrigerate AVONEX prefilled syringes and autoinjectors at 2°C to 8°C (36°F to 46°F) in the original carton to protect from light. DO NOT FREEZE. Once removed from the refrigerator, allow prefilled syringes and autoinjectors to warm to room temperature (about 30 minutes). Do not use external heat sources such as hot water to warm AVONEX.

Should refrigeration be unavailable, a prefilled syringe or autoinjector may be stored at room temperature up to 25°C (77°F) for a period up to 7 days. DO NOT EXPOSE TO HIGH TEMPERATURES. Once the product is removed from the refrigerator, it must not be stored above 25°C (77°F). If the product has been exposed to conditions other than those recommended, DISCARD THE PRODUCT and DO NOT USE.

Do not use beyond the expiration date.

AVONEX Prefilled Syringe and AVONEX PEN contain natural rubber latex which may cause allergic reactions.

17 PATIENT COUNSELING INFORMATION

See FDA-approved patient labeling (Medication Guide and Patient's Instructions for Use).

Instruct patients to carefully read the supplied AVONEX Medication Guide and caution patients not to change the AVONEX dose or schedule of administration without medical consultation.

Inform patients that the tip cap of the AVONEX Prefilled Syringe and AVONEX PEN contains natural rubber latex which may cause allergic reactions.

Instruction on Self-injection Technique and Procedures

Provide appropriate instruction for methods of self-injection of AVONEX, including careful review of the AVONEX Medication Guide. Instruct patients in the use of aseptic technique when administering AVONEX.

Inform patients that an appropriately qualified healthcare professional should show them or their caregiver how to prepare and inject AVONEX before administering the first dose. An appropriately qualified healthcare professional should watch the first AVONEX injection given. Tell patients not to re-use needles or syringes and instruct patients on safe disposal procedures. Inform patients to dispose of used needles and syringes in a puncture-resistant container and instruct the patient regarding safe disposal of full containers.

Advise patients:

- of the importance of rotating areas of injection with each dose to minimize the likelihood of injection site reactions. [see Warnings and Precautions (5.4) and Choose an Injection Site section of the Medication Guide].
- NOT to inject area of the body where the skin is irritated, reddened, bruised, infected or scarred in any way
- to check the injection site after 2 hours for redness, swelling, or tenderness
- contact their healthcare provider if they have a skin reaction and it does not clear up in a few days

Pregnancy

Advise patients to notify their healthcare provider if they become pregnant during treatment or plan to become pregnant [see Use in Specific Populations (8.1)].

Depression

Advise patients of the symptoms of depression, suicidal ideation, or psychotic disorders as they have been reported with the use of AVONEX and instruct patients to report them immediately to their physician [see Warnings and Precautions (5.1)].

Liver Disease

Advise patients that severe hepatic injury, including hepatic failure, has been reported during the use of AVONEX. Advise patients of symptoms of hepatic dysfunction, and instruct patients to report them immediately to their physician [see Warnings and Precautions (5.2)].

Allergic Reactions and Anaphylaxis

Advise patients of the symptoms of allergic reactions and anaphylaxis, and instruct patients to seek immediate medical attention if these symptoms occur [see Warnings and Precautions (5.3)].

Injection Site Reactions Including Necrosis

Advise patients that injection site reactions can occur and that the reactions can include injection site necrosis. Instruct patients to report promptly any break in the skin that is associated with blue-black discoloration, swelling, or drainage of fluid from the injection site [see Warnings and Precautions (5.4)].

Congestive Heart Failure

Advise patients that worsening of pre-existing congestive heart failure has been reported in patients using AVONEX. Advise patients of symptoms of worsening cardiac condition, and instruct patients to report them immediately to their physician [see Warnings and Precautions (5.5)].

Pulmonary Arterial Hypertension

Inform patients that PAH has occurred in patients treated with interferon beta products, including AVONEX. Instruct patients to promptly report any new symptoms such as new or increasing fatigue or shortness of breath to their healthcare provider [see Warnings and Precautions (5.8)].

Seizures

Advise patients that seizures have been reported in patients using AVONEX. Instruct patients to report seizures immediately to their physician [see Warnings and Precautions (5.9)].

Flu-like Symptoms

Inform patients that flu-like symptoms are common following initiation of therapy with AVONEX [see Dosage and Administration (2.3) and Adverse Reactions (6)]. Advise patients that starting with a lower dose than 30 micrograms and increasing the dose over 3 weeks reduces the incidence and severity of flu-like symptoms.

41613-07

Manufactured by:

Biogen Inc.

Cambridge, MA 02142 USA

U.S. License #1697

1-800-456-2255

AVONEX is a registered trademark of Biogen.

© Biogen 1996-2023. All rights reserved.

MEDICATION GUIDE
AVONEX® (a-vuh-necks)
(interferon beta-1a) Injection for intramuscular use

Read this Medication Guide before you start using AVONEX, and each time you get a refill. There may be new information. This information does not take the place of talking with your healthcare provider about your medical condition or your treatment.

What is the most important information I should know about AVONEX?
AVONEX can cause serious side effects. Tell your healthcare provider right away if you have any of the symptoms listed below while taking AVONEX.
1. Depression, suicidal thoughts, hallucinations or other behavioral health problems. Some people taking AVONEX may develop mood or behavior problems including:

- irritability (getting upset easily)
- depression (feeling hopeless or feeling bad about yourself)
- nervousness
- anxiety
- aggressive behavior
- thoughts of hurting yourself or suicide
- hearing or seeing things that others do not hear or see (hallucinations)

If you have any of these mood or behavior problems, your healthcare provider may tell you to stop taking AVONEX.
2. Liver problems, or worsening of liver problems including liver failure and death. Tell your healthcare provider right away if you have any of these symptoms:

- nausea
- loss of appetite

- tiredness
- dark colored urine and pale stools

- yellowing of your skin or the white part of your eye
- bleeding more easily than normal

- confusion
- sleepiness

During your treatment with AVONEX you will need to see your healthcare provider regularly and have regular blood tests to check for side effects. Tell your healthcare provider about all the medicines you take and if you drink alcohol before you start taking AVONEX.

3. Serious allergic and skin reactions. Serious allergic and skin reactions can happen when you take AVENOX. Symptoms of serious allergic and skin reactions may include:

- itching
- swelling of the face, eyes, lips, tongue or throat
- trouble breathing
- anxiousness
- feeling faint
- skin rash, hives, sores in your mouth, or your skin blisters and peels

Get emergency help right away if you have any of these symptoms. Talk to your healthcare provider before taking another dose of AVONEX.

What is AVONEX?
AVONEX is a prescription medicine used to treat relapsing forms of multiple sclerosis (MS), to include clinically isolated syndrome, relapsing-remitting disease, and active secondary progressive disease in adults.
It is not known if AVONEX is safe and effective in children.

Do not take AVONEX if you:

- are allergic to interferon beta or any of the ingredients in AVONEX. See the end of this Medication Guide for a complete list of ingredients in AVONEX.

Before taking AVONEX, tell your healthcare provider about all of your medical conditions, including if you:

- are being treated for a mental illness or had treatment in the past for any mental illness, including depression and suicidal behavior.
- have or had bleeding problems or blood clots.
- have or had low blood cell counts.
- have or had liver problems.
- have or had seizures. (epilepsy).
- have or had heart problems.
- have or had thyroid problems.
- have or had any kind of autoimmune disease (where the body's immune system attacks the body's own cells).
- drink alcohol.
- have or have had an allergic reaction to rubber or latex. The tip cap of the AVONEX prefilled syringe and prefilled autoinjector Pen contain natural rubber latex.
- are pregnant or plan to become pregnant. It is not known if AVONEX can harm your unborn baby.
- are breastfeeding or plan to breastfeed. AVONEX may pass into your breastmilk. Talk with your healthcare provider about the best way to feed your baby if you take AVONEX.

Tell your healthcare provider about all the medicines you take, including prescription and over-the-counter medicines, vitamins, and herbal supplements.

How should I use AVONEX?

- See the Instructions for Use for detailed instructions for preparing and injecting your dose of AVONEX.
- A healthcare provider should show you how to prepare your dose of AVONEX and how to inject your AVONEX before you use it for the first time.
- A healthcare provider or nurse should watch the first AVONEX injection you give yourself.
- AVONEX is given 1 time each week by injection into the muscle (intramuscular injection).
- Inject AVONEX exactly as your healthcare provider tells you.
- Your healthcare provider will tell you how much AVONEX to inject and how often to inject AVONEX. Do not inject more than your healthcare provider tells you to.
- Do not change your dose unless your healthcare provider tells you to.
- Change (rotate) your injection site you choose with each injection. This will help decrease the chance that you will have an injection site reaction.
- Do not inject into an area of the body where the skin is irritated, reddened, bruised, infected or scarred in any way.
- AVONEX comes as a:
  - Single-dose prefilled syringe (can be used with the AVOSTARTGRIP™ titration kit)
  - Single-dose prefilled autoinjector Pen (AVONEX PEN®)
- After 2 hours check your injection site for redness, swelling or tenderness. If you have a skin reaction and it does not clear up in a few days, contact your healthcare provider.

Your healthcare provider will decide which one is best for you.
Always use a new, unopened AVONEX single-dose prefilled syringe or single-dose prefilled autoinjector pen for each intramuscular injection.

What are the possible side effects of AVONEX?
AVONEX can cause serious side effects including:

- See “What is the most important information I should know about AVONEX?”
- Injection site reactions. AVONEX may cause redness, pain, itching, or swelling at the place where your injection was given. Call your healthcare provider right away if an injection site becomes swollen and painful or the area looks infected. You may have a skin infection or an area of severe skin damage (necrosis) requiring treatment by a healthcare provider.
- Heart problems, including heart failure. Some people who did not have a history of heart problems developed heart muscle problems or congestive heart failure after taking AVONEX. If you already have heart failure, AVONEX may cause your heart failure to get worse. Call your healthcare provider right away if you have worsening symptoms of heart failure such as shortness of breath or swelling of your lower legs or feet while using AVONEX.
  - Some people using AVONEX may have other heart problems including:
    - low blood pressure
    - fast or abnormal heart beat
    - chest pain
    - heart attack or a heart muscle problem (cardiomyopathy)
- Blood problems. AVONEX can affect your bone marrow and cause low red and white blood cell, and platelet counts. In some people, these blood cell counts may fall to dangerously low levels. If your blood cell counts become very low, you can get infections and problems with bleeding and bruising.
- Thrombotic microangiopathy (TMA). TMA is a condition that involves injury to the smallest blood vessels in your body. TMA can also cause injury to your red blood cells (the cells that carry oxygen to your organs and tissues) and your platelets (cells that help your blood clot) and can sometimes lead to death. Your healthcare provider may tell you to stop taking AVONEX if you develop TMA.
- Pulmonary arterial hypertension. Pulmonary arterial hypertension can occur with interferon beta products, including AVONEX. Symptoms may include new or increasing fatigue or shortness of breath. Contact your healthcare provider right away if you develop these symptoms.
- Seizures. Some people have had seizures while taking AVONEX, including people who have never had seizures before. Tell your healthcare provider right away if you have a seizure.
- Autoimmune diseases. Problems with easy bleeding or bruising (idiopathic thrombocytopenia), thyroid gland problems (hyperthyroidism and hypothyroidism), and autoimmune hepatitis have happened in some people who use AVONEX.

The most common side effects of AVONEX include:

- Flu-like symptoms. Most people who take AVONEX have flu-like symptoms especially early during the course of therapy. Usually, these symptoms last for a day after the injection. Symptoms may include:
  - muscle aches
  - fever
  - tiredness
  - chills

You may be able to manage these flu-like symptoms by taking over-the-counter pain and fever reducers. Talk with your healthcare provider about ways to help if you develop flu-like symptoms while taking AVONEX.
These are not all of the possible side effects of AVONEX.
Call your doctor for medical advice about side effects. You may report side effects to FDA at 1-800-FDA-1088.

How should I store AVONEX?

- Store AVONEX in the refrigerator between 36°F to 46°F (2°C to 8°C).
- Do not freeze AVONEX. Do not use AVONEX that has been frozen.
- If you cannot refrigerate your AVONEX PEN and AVONEX prefilled syringes, you can store your AVONEX PEN and AVONEX prefilled syringes at room temperature up to 77°F (25°C) for up to 7 days.
- Do not store AVONEX above 77°F (25°C). Do not use AVONEX that is stored at temperatures higher than 77°F (25°C). Throw it away in a FDA-cleared sharps disposal container.
- Keep AVONEX in the original carton to protect it from light.
- Do not use AVONEX past the expiration date.

Keep AVONEX prefilled syringes, pens, and all other medicines out of the reach of children.

General information about the safe and effective use of AVONEX.
Medicines are sometimes prescribed for purposes other than those listed in a Medication Guide. Do not use AVONEX for a condition for which it was not prescribed. Do not give AVONEX to other people, even if they have the same symptoms that you have. It may harm them. You can ask your pharmacist or healthcare provider for information about AVONEX that is written for health professionals.

What are the ingredients in AVONEX?
Active ingredient: interferon beta-1a
Inactive ingredients:

- Single-Dose Prefilled Syringe: arginine hydrochloride, glacial acetic acid, polysorbate 20, sodium acetate trihydrate in water for inject]tion.
- Single-Dose Prefilled Autoinjector Pen: arginine hydrochloride, glacial acetic acid, polysorbate 20, sodium acetate trihydrate in water for injection.

Manufactured by:
Biogen Inc. Cambridge, MA 02142 USA
U.S. License #1697
AVONEX is a registered trademark of Biogen. © Biogen 1996-2023. All rights reserved.
For more information, call 1-1-800-456-2255.

This Medication Guide has been approved by the U.S. Food and Drug Administration.

Revised: 7/2023

INSTRUCTIONS FOR USE

AVONEX PEN® (a-vuh-necks)

(interferon beta-1a)

injection for intramuscular use

single-dose prefilled autoinjector pen

Read the Instructions for Use before you start using AVONEX and each time you get a refill. There may be new information. This information does not take the place of talking to your healthcare provider about your medical condition or your treatment.

Your healthcare provider should show you or your caregiver how to prepare the dose of AVONEX and how to inject your AVONEX PEN the right way before AVONEX PEN is used for the first time. Your healthcare provider or nurse should watch you inject the dose of AVONEX the first time AVONEX PEN is used.

Important information: The tip of the cap of the AVONEX PEN is made of natural rubber latex. Tell your healthcare provider if you are allergic to rubber or latex.

How should I store AVONEX?

- Store AVONEX in the refrigerator between 36°F to 46°F (2°C to 8°C).
- Do not freeze AVONEX. Do not use AVONEX that has been frozen.
- If you cannot refrigerate your AVONEX PEN, you can store your AVONEX PEN at room temperature up to 77°F (25°C) for up to 7 days.
- Do not store AVONEX above 77°F (25°C). Do not use AVONEX that is stored at temperatures higher than 77°F (25°C).
- Throw AVONEX away in an FDA-cleared sharps disposal container if it has not been stored as stated above. (See After the AVONEX injection section at the end of this Instructions for Use.)
- Keep AVONEX in the original carton to protect it from light.

Preparing the AVONEX PEN:

- Find a well lit, clean, flat work surface like a table and collect all the supplies you will need to give yourself or receive an injection.
- Take 1 AVONEX PEN Administration Dose Pack out of the refrigerator about 30 minutes before you plan on injecting the AVONEX dose to allow it to reach room temperature. Do not use external heat sources such as hot water to warm the AVONEX PEN.
- Check the expiration date printed on the AVONEX PEN, AVONEX PEN Administration Dose Pack carton, and the outer carton. Do not use the AVONEX PEN past the expiration date.
- Wash your hands with soap and water.

Supplies you will need to give the AVONEX PEN injection:

- 1 AVONEX Administration Dose Pack that contains:
  - 1 AVONEX PEN
  - a 25 gauge, 5/8 inch long sterile needle
  - 1 AVONEX PEN cover
- 1 alcohol wipe
- 1 gauze pad
- 1 adhesive bandage
- a puncture resistant container for disposal of used AVONEX PEN and needle

Identifying parts of the AVONEX PEN (See Figure A).

Single-Dose Administration Dose Pack Contents – AVONEX PEN, Supplied Needle and AVONEX PEN Cover

(Figure A)

Preparing the AVONEX PEN injection:

Step 1: Hold the AVONEX PEN with the white tamper-evident cap (cap) pointing up (See Figure B).

- Check that the cap is intact and has not been removed. If the cap has been removed or is not tightly attached, do not use it. Throw it away and get a new AVONEX PEN. (See After the AVONEX injection section at the end of this Instructions for Use.)

(Figure B)

Step 2: With your other hand, grasp the cap and bend it at a 90° angle until the cap snaps off (See Figure C).

- After the cap comes off, you will see the glass tip of the syringe. Do not touch the glass tip of the syringe (See Figure D).

(Figure C)
(Figure D)

Step 3: Place the AVONEX PEN down on a flat work surface.

Step 4: Pull off the sterile foil from the needle cover (See Figure E).

- Only use the needle that comes with your AVONEX PEN.

(Figure E)

Step 5: Hold the AVONEX PEN with the glass syringe tip pointing up. Press the needle onto the AVONEX PEN glass syringe tip (See Figure F).

(Figure F)

Step 6: Gently turn the needle to the right (clockwise) until it is firmly attached (See Figure G).

- If the needle is not firmly attached, it may leak, and you may not get your full dose of AVONEX.

(Figure G)

- Do not remove the plastic cover from the needle (See Figure H).

(Figure H)

Step 7: Hold the body of the AVONEX PEN in 1 hand with the needle and needle cover pointing away from you and other people. Do not remove the plastic cover from the needle (See Figure I).

(Figure I)

Step 8: Using your other hand, hold onto the injector shield (grooved area) tightly and quickly pull up on the injector shield until the injector shield covers the needle all the way.

- The plastic needle cover will “pop” off after the injector shield has been fully extended (See Figure J).

(Figure J)

- When the injector shield is extended the right way, you will see a small blue rectangular area next to the oval medicine display window (See Figure K).

(Figure K)

Step 9: Check the oval medicine display window and make sure the AVONEX is clear and colorless (See Figure L).
You might see air bubbles in the oval medicine display window. This is normal and will not affect your dose.

- Do not use AVONEX PEN if the liquid is colored, cloudy, or contains any lumps or particles. Throw away the AVONEX PEN in an FDA-cleared sharps container and get a new one, then repeat steps 1 to 9. (See After the AVONEX injection section at the end of this Instructions for Use .)

(Figure L)

Giving the AVONEX injection:

- Your healthcare provider should show you or your caregiver how to prepare the dose of AVONEX and how to inject your AVONEX PEN the right way before AVONEX PEN is used for the first time. Your healthcare provider or nurse should watch you inject the dose of AVONEX the first time AVONEX PEN is used.
- Inject your AVONEX PEN exactly as your healthcare provider has shown you.
- AVONEX PEN is injected into the muscle (intramuscularly).
- AVONEX PEN should be injected into the upper, outer thigh (See Figure M).
- Change (rotate) injection sites for each dose. Do not use the same injection site for each injection.
- Do not inject into an area of the body where the skin is irritated, reddened, bruised, infected or scarred in any way.
- Do not push down on the injector shield and the blue activation button at the same time until you are ready to give your injection.

Figure M

Step 10: Choose an injection site and wipe the skin with an alcohol wipe (See Figure N). Let the injection site dry before injecting the dose.

- Do not touch this area again before giving the injection.

(Figure N)

Step 11: Place the AVONEX PEN on the injection site (See Figure O).

(Figure O)

Step 12: Hold the body of the AVONEX PEN at a 90º angle to the injection site, and make sure you can see the window (See Figure P).

(Figure P)

Step 13: Keeping your fingers away from the blue activation button, firmly push the body of the AVONEX PEN down against the thigh to release the safety lock (See Figure Q). Do not lift the AVONEX PEN off the injection site.

- Check to make sure the safety lock has been released. You will know the safety lock is released when the small blue rectangular area above the oval medicine display window is gone (See Figure R).

(Figure Q)
(Figure R)

Step 14: Continue to firmly maintain pressure and push down on the AVONEX PEN against the injection site, then push down on the blue activation button with your thumb (See Figure S). Keep the AVONEX PEN pushed down against the injection site and slowly count to 10.

- You will hear a “click” when the injection starts. If you do not hear a “click”, your injection was not given the right way.
- If this happens, make sure that the injector shield is extended, the safety lock is completely released, and that you are firmly maintaining pressure and pushing down against the injection site. Press the blue activation button with your thumb again. If you still do not hear a “click”, call Biogen at 1-800-456-2255.

(Figure S)

Step 15: After you count to 10, pull the AVONEX PEN straight out of the skin (See Figure T). Use the gauze pad to apply pressure to the injection site for a few seconds or rub gently in a circular motion.
• If you see blood after you press the injection site for a few seconds, wipe it off with the gauze pad and apply an adhesive bandage.

(Figure T)

Step 16: Check the circular display window on the AVONEX PEN to make sure that it is yellow. This is to be sure that you have been given your full dose (See Figure U).

- If you did not receive your full dose of AVONEX, throw away the AVONEX PEN in a FDA-cleared sharps disposal container and call your healthcare provider. Do not re-use the AVONEX PEN.

(Figure U)

Step 17: Do not hold the AVONEX PEN cover with your hands. Place the AVONEX PEN cover on a flat work surface. Line up the exposed needle with the hole of the AVONEX PEN cover, and insert directly into the opening (See Figure V).

(Figure V)

Step 18: Firmly press the AVONEX PEN down until you hear a “click” to seal the needle (See Figure W). You may need to hold both hands around the AVONEX PEN body to snap the AVONEX PEN cover into place.

(Figure W)

After the AVONEX injection:

Throw Away your AVONEX:

- Put your used needles and PENS in an FDA-cleared sharps disposal container right away after use. Do not throw away (dispose of) loose needles and syringes in your household trash.
- If you do not have an FDA-cleared sharps disposal container, you may use a household container that is:
  - made of a heavy-duty plastic,
  - can be closed with a tight-fitting, puncture-resistant lid, without sharps being able to come out,
  - upright and stable during use,
  - leak-resistant, and
  - properly labeled to warn of hazardous waste inside the container.
- When your sharps disposal container is almost full, you will need to follow your community guidelines for the right way to dispose of your sharps disposal container. There may be state or local laws about how you should throw away used needles and syringes. For more information about safe sharps disposal, and for specific information about sharps disposal in the state that you live in, go to the FDA's website at: http://www.fda.gov/safesharpsdisposal
- Do not dispose of your used sharps disposal container in your household trash unless your community guidelines permit this. Do not recycle your used sharps disposal container.

Check Your Injection Site:

- After 2 hours, check the injection site for redness, swelling or tenderness. If you have a skin reaction and it does not clear up in a few days, contact your healthcare provider.

General information about the safe and effective use of AVONEX PEN

- Always use a new AVONEX PEN and needle for each injection. Do not re-use your AVONEX PEN or needle.
- Do not share your AVONEX PEN or needles.
- Keep AVONEX PEN and needles and all medicines out of the reach of children.

This Instructions for Use has been approved by the U.S. Food and Drug Administration.

Manufactured by:

Biogen Inc.

Cambridge, MA 02142 USA

U.S. License # 1697

1-800-456-2255

AVONEX is a registered trademark of Biogen.

©Biogen 1996-2020. All rights reserved.

Revised: 03/2020

41610-03

INSTRUCTIONS FOR USE

AVONEX® (a-vuh-necks)

(interferon beta-1a)

injection for intramuscular use

single-dose prefilled syringe

Read the Instructions for Use before you start using AVONEX and each time you get a refill. There may be new information. This information does not take the place of talking to your healthcare provider about your medical condition or your treatment.

Important information: The tip of the cap of the AVONEX prefilled syringe is made of natural rubber latex. Tell your healthcare provider if you are allergic to rubber or latex.

How should I store AVONEX?

- Store AVONEX in the refrigerator between 36°F to 46°F (2°C to 8°C).
- Do not freeze AVONEX. Do not use AVONEX that has been frozen.
- If you cannot refrigerate your AVONEX prefilled syringes, you can store your AVONEX prefilled syringes at room temperature up to 77°F (25°C) for up to 7 days.
- Do not store AVONEX above 77°F (25°C). Do not use AVONEX that is stored at temperatures higher than 77°F (25°C).
- Throw AVONEX away in an FDA-cleared sharps disposal container if it has not been stored as stated above. (See After the AVONEX injection section at the end of this Instructions for Use.)
- Keep AVONEX in the original carton to protect it from light.

Supplies you will need for the AVONEX injection:

- 1 AVONEX Administration Dose Pack that contains:
  - 1 AVONEX prefilled syringe
  - 23 gauge, 1¼ inch long sterile needle
- 1 alcohol wipe
- 1 gauze pad
- 1 adhesive bandage
- a puncture resistant container for disposal of used syringes and needles

Preparing the dose of AVONEX:

- Find a well-lit, clean, flat work surface like a table and collect all the supplies you will need to give yourself or receive an injection.
- Take 1 AVONEX Administration Dose Pack out of the refrigerator about 30 minutes before you plan on injecting the AVONEX dose to allow it to reach room temperature. Do not use external heat sources such as hot water to warm the AVONEX prefilled syringe.
- Check the expiration date printed on AVONEX prefilled syringe, AVONEX Administration Dose Pack, and the outer carton. Do not use AVONEX prefilled syringe past the expiration date.
- Wash your hands with soap and water.

Identifying parts of the AVONEX prefilled syringe (See Figure A):

Preparing the AVONEX injection:

Step 1: Hold the AVONEX prefilled syringe with the cap pointing down and with the 0.5 mL mark at eye level (See Figure A).

- Check the syringe:
  - The syringe should not have any cracks or damage.
  - Check that the cap is intact and has not been removed.
  - The amount of liquid in the syringe should be at or very close to the 0.5 mL mark.
  - AVONEX should look clear, colorless, and should not have any particles in it.
- Do not use the AVONEX prefilled syringe if:
  - the syringe is cracked or damaged
  - the solution is cloudy, colored, or has lumps or particles in it
  - the cap has been removed or is not tightly attached or
  - there is not enough liquid in the syringe
  If you cannot use that syringe, you will need to get a new syringe. Contact Biogen at 1-800-456-2255.

(Figure A)

Step 2: With 1 hand, hold the AVONEX prefilled syringe right under the cap and with the cap pointing up (See Figure B).

- Make sure you are holding the AVONEX prefilled syringe by the ridged part, directly under the cap.

(Figure B)

Step 3: With the other hand, grasp the cap and bend it at a 90º angle until the cap snaps off (See Figure C and Figure D).

(Figure C)
(Figure D)

Step 4: Open the sterile needle package and take out the covered needle. Hold the AVONEX prefilled syringe with the glass syringe tip pointing up. Press the needle on the AVONEX prefilled syringe glass tip (See Figure E).

(Figure E)

Step 5: Gently turn the needle to the right (clockwise) until it is tight and firmly attached (See Figure F).

- If the needle is not firmly attached, it may leak and you may not get your full dose of AVONEX.
- Do not remove the plastic cover from the needle.

(Figure F)

Giving the AVONEX injection:

- Your healthcare provider should show you or a caregiver how to prepare and inject the dose of AVONEX before AVONEX prefilled syringe is used for the first time. Your healthcare provider or nurse should watch you inject the dose of AVONEX the first time AVONEX prefilled syringe is used.
- Inject your AVONEX exactly as your healthcare provider has shown you.
- AVONEX is injected into the muscle (intramuscularly).
- AVONEX should be injected into the thigh or upper arm (See Figures G and H).
- Change (rotate) your injection sites for each dose. Do not use the same injection site for each injection.
- Do not inject into an area of the body where the skin is irritated, reddened, bruised, infected or scarred in any way.

Step 6: Choose an injection site and wipe the skin with an alcohol wipe (See Figures G and H). Let the injection site dry before injecting the dose.

- Do not touch this area again before giving the injection.

(Figure G)

(Figure H)

Step 7: Pull the protective cover straight off the needle (See Figure I). Do not twist the cover off.

(Figure I)

Step 8: With 1 hand, stretch the skin out around the injection site. With the other hand, hold the syringe like a pencil. Use a quick dart-like motion and insert the needle at a 90 degree angle, through the skin and into the muscle (See Figure J). After the needle is in, let go of the skin.

(Figure J)

Step 9: Slowly push the plunger down until the syringe is empty (See Figure K).

(Figure K)

Step 10: Pull the needle out of the skin (See Figure L). Press down on the injection site with the gauze pad for a few seconds or rub gently in a circular motion.

- If you see blood after you press the injection site for a few seconds, wipe it off with the gauze pad and apply an adhesive bandage.

(Figure L)

After the AVONEX injection:

- Do not recap the needle. Recapping the needle can lead to a needle stick injury.
- Put your used needles and syringes in an FDA-cleared sharps disposal container right away after use. Do not throw away (dispose of) loose needles and syringes in your household trash.
- If you do not have an FDA-cleared sharps disposal container, you may use a household container that is:
  - made of a heavy-duty plastic,
  - can be closed with a tight-fitting, puncture-resistant lid, without sharps being able to come out,
  - upright and stable during use,
  - leak-resistant, and
  - properly labeled to warn of hazardous waste inside the container.
- When your sharps disposal container is almost full, you will need to follow your community guidelines for the right way to dispose of your sharps disposal container. There may be state or local laws about how you should throw away used needles and syringes. For more information about safe sharps disposal, and for specific information about sharps disposal in the state that you live in, go to the FDA's website at: http://www.fda.gov/safesharpsdisposal
- Do not dispose of your used sharps disposal container in your household trash unless your community guidelines permit this. Do not recycle your used sharps disposal container.

Check Your Injection Site:

- After 2 hours, check the injection site for redness, swelling or tenderness. If you have a skin reaction and it does not clear up in a few days, contact your healthcare provider.

General information about the safe and effective use of AVONEX

- Always use a new AVONEX prefilled syringe and needle for each injection. Do not re-use your AVONEX prefilled syringe or needles.
- Do not share your AVONEX prefilled syringe or needles.
- Keep the AVONEX prefilled syringe and needles and all medicines out of the reach of children.

This Instructions for Use has been approved by the U.S. Food and Drug Administration.

Manufactured by:

Biogen Inc.

Cambridge, MA 02142 USA

U.S. License # 1697

1-800-456-2255

AVONEX is a registered trademark of Biogen.

©Biogen 1996-2020. All rights reserved.

Revised: 03/2020

41611-03

Instructions for Use

AVOSTARTGRIP® Titration Kit

Use with AVONEX® (interferon beta-1a) Prefilled Syringe Only

Read the Instructions for Use before you start using AVONEX and each time you get a refill. There may be new information. This information does not take the place of talking to your healthcare provider about your medical condition or your treatment.

Preparing the AVONEX Prefilled Syringe:

- Find a well lit, clean, flat work surface like a table and collect all the supplies you will need to give yourself or receive an injection.
- Take 1 AVONEX Administration Dose Pack out of the refrigerator about 30 minutes before you plan on injecting the AVONEX dose to allow it to reach room temperature. Do not use external heat sources such as hot water to warm the AVONEX prefilled syringe.
- Check the expiration date printed on the AVONEX prefilled syringe, AVONEX prefilled syringe Administration Dose Package carton, and the outer carton. Do not use the AVONEX prefilled syringe past the expiration date.
- Wash your hands with soap and water.

Supplies you will need for the AVONEX injection:

- 1 AVONEX Administration Dose Pack that contains:
  - 1 AVONEX prefilled syringe
  - 23 gauge, 1¼ inch long sterile needle
- 1 alcohol wipe
- 1 gauze pad
- 1 adhesive bandage
- a puncture resistant container for disposal of used syringes and needles

Identifying parts of the AVONEX prefilled syringe (See Figure A):

Preparing the AVONEX injection:

Step 1: Hold the AVONEX prefilled syringe with the cap pointing down and with the 0.5 mL mark at eye level (See Figure A).

- Check the syringe:
  - The syringe should not have any cracks or damage.
  - Check that the cap is intact and has not been removed.
  - The amount of liquid in the syringe should be at or very close to the 0.5 mL mark.
  - AVONEX should look clear, colorless, and should not have any particles in it.
- Do not use the AVONEX prefilled syringe if:
  - the syringe is cracked or damaged
  - the solution is cloudy, colored, or has lumps or particles in it
  - the cap has been removed or is not tightly attached or
  - there is not enough liquid in the syringe

Do not use that syringe. Get a new syringe. Contact MS ACTIVESOURCE at 1-800-456-2255.

(Figure A)

Step 2: With 1 hand, hold the AVONEX prefilled syringe right under the cap and with the cap pointing up (See Figure B).

- Make sure you are holding the AVONEX prefilled syringe by the ridged part, directly under the cap.

(Figure B)

Step 3: With the other hand, grasp the cap and bend it at a 90º angle until the cap snaps off (See Figure C and Figure D).

(Figure C)
(Figure D)

Step 4: Open the sterile needle package and take out the covered needle. Hold the AVONEX prefilled syringe with the glass syringe tip pointing up. Press the needle on the AVONEX prefilled syringe glass tip (See Figure E).

(Figure E)

Step 5: Gently turn the needle forward (clockwise) until it is tight and firmly attached (See Figure F).

- If the needle is not firmly attached, it may leak and you may not get your full dose of AVONEX.
- Do not remove the plastic cover from the needle.

(Figure F)

Using the AVONEX prefilled syringe with the AVOSTARTGRIP titration kit:

- Your AVONEX dose may be titrated over 3 weeks by using AVONEX prefilled syringe with the AVOSTARTGRIP titration kit. The AVOSTARTGRIP is used for giving the week 1, 2, and 3 (¼, ½, ¾) injections.
  - Week 1: ¼ dose (white device)
  - Week 2: ½ dose (yellow device)
  - Week 3: ¾ dose (purple device)
  - Week 4: a full dose
- The 3 AVOSTARTGRIP devices are for single-use only with the AVONEX prefilled syringe. Do not re-use the AVONEX prefilled syringe and AVOSTARTGRIP devices.
- You must prepare the AVONEX prefilled syringe and needle before you put it into the AVOSTARTGRIP device. Follow steps 1 to 5 above to prepare the AVONEX prefilled syringe.

Identifying the parts of AVOSTARTGRIP titration kit (See Figure G):

(Figure G)

- AVOSTARTGRIP has a “collar” on top of the device that will stop the syringe from injecting a full dose (See Figure H). The “collar” makes sure that you do not get the full dose of AVONEX.

(Figure H)

Attaching the AVOSTARTGRIP device:

Step 6: Choose the right AVOSTARTGRIP titration device for your weekly dose.

- Week 1 Injection: Choose the white device to give ¼ dose (See Figure I).

(Figure I)

- Week 2 Injection: Choose the yellow device to give ½ dose (See Figure J).

(Figure J)

- Week 3 Injection: Choose the purple device to give ¾ dose (See Figure K).

(Figure K)

Step 7: Put the right AVOSTARTGRIP device on a flat surface with the door open (See Figure L).

(Figure L)

Step 8: Line up the AVONEX prefilled syringe over the AVOSTARTGRIP device with the plunger pointing to the left and the needle pointing to the right (See Figure M).

(Figure M)

Step 9: Push the AVONEX prefilled syringe down into the AVOSTARTGRIP device until both ends “snap” into place (See Figure N).

(Figure N)

Step 10: Using two fingers, push the door down until it closes over the AVONEX prefilled syringe (See Figure O).

- You will hear a “snap” when the door is closed the right way. Do not open door after it is closed.

(Figure O)

Step 11: Check to make sure that the AVONEX prefilled syringe is in the AVOSTARTGRIP device the right way and that the door is tightly closed.

Giving the AVONEX injection:

- Your healthcare provider should show you or a caregiver how to prepare and inject the dose of AVONEX before AVONEX prefilled syringe is used for the first time. Your healthcare provider or nurse should watch you inject the dose of AVONEX the first time AVONEX prefilled syringe is used.
- Inject your AVONEX exactly as your healthcare provider has shown you.
- AVONEX is injected into the muscle (intramuscularly).
- AVONEX should be injected into the thigh or upper arm (See Figures P and Q).
- Change (rotate) your injection sites for each dose. Do not use the same injection site for each injection.
- Do not inject into an area of the body where the skin is irritated, reddened, bruised, infected or scarred in any way.

Step 12: Choose an injection site and wipe the skin with an alcohol wipe (See Figures P and Q). Let the injection site dry before injecting the dose.

- Do not touch this area again before giving the injection.

(Figure P)

(Figure Q)

Step 13: Pull the protective cover straight off the needle (See Figure R). Do not twist the cover off.

(Figure R)

Step 14: With 1 hand, stretch the skin out around the injection site. With the other hand, hold the syringe like a pencil. Use a quick dart-like motion and insert the needle at a 90º angle, through the skin and into the muscle (See Figure S). Once the needle is in, let go of the skin.

(Figure S)

Step 15: Make sure that you push the plunger all the way down until it touches the collar (See Figure T).

(Figure T)

Step 16: Pull the needle out of the skin (See Figure U). Press down on the injection site with the gauze pad for a few seconds or rub gently in a circular motion.

- If you see blood after you press the injection site for a few seconds, wipe it off with gauze and apply an adhesive bandage.

(Figure U)

After the AVONEX injection:

Do not recap the needle. Recapping the needle can lead to a needle stick injury.

- Throw away the used AVONEX prefilled syringes, AVOSTARTGRIP devices, and needles in a sharps container or some type of hard plastic or metal container with a screw cap such as a detergent bottle or coffee can. Check with your healthcare provider about the right way to throw away the container. There may be local or state laws about how to throw away used AVONEX prefilled syringes, AVOSTARTGRIP devices, and needles. Do not throw away used AVONEX prefilled syringes, AVOSTARTGRIP devices, and needles in household trash or recycling bins.
- After 2 hours, check the injection site for redness, swelling or tenderness. If you have a skin reaction and it does not clear up in a few days, contact your healthcare provider.

General information about the safe and effective use of AVONEX

- Always use a new AVONEX prefilled syringe, AVOSTARTGRIP device, and needle for each injection. Do not re-use your AVONEX prefilled syringe, AVOSTARTGRIP device, or needles.
- Do not share your AVONEX prefilled syringe, AVOSTARTGRIP device, or needles.
- Keep the AVONEX prefilled syringe, AVOSTARTGRIP device, and needles out of the reach of children.
- You can use the table below to keep track of your weekly injections.

This Instructions for Use has been approved by the U.S. Food and Drug Administration.

Revised 09/2016
Manufactured for:
Biogen Inc.
250 Binney Street
Cambridge, MA 02142 USA
©2012-2016 Biogen. All rights reserved.
1-800-456-2255

I11073-05

Principal Display Panel - 30 mcg Carton Label

NDC 59627-003-01

Avonex Pen®

(interferon beta-1a)

Injection

30 mcg/0.5 mL Single-Use Prefilled Autoinjector

For Intramuscular Injection

Once a Week

Avonex Pen® Administration Dose Pack

ATTENTION PHARMACIST: Each patient is required to receive the enclosed Medication Guide.

Store refrigerated at 2-8°C (36-46°F).

Do not freeze or expose to high temperatures. Protect from light.

The recommended dosage of Avonex® is 30 mcg injected intramuscularly
once weekly. See package insert for full prescribing information.

This Product Contains Dry Natural Rubber.

Rx only

Principal Display Panel - 30 mcg Carton Label

NDC 59627-002-06

Avonex®
(interferon beta-1a)
Injection

30 mcg/0.5 mL Single-Use Prefilled Syringe

For Intramuscular Injection

Once a Week

Avonex® Administration Dose Pack

ATTENTION PHARMACIST: Each patient is required
to receive the enclosed Medication Guide.

Store refrigerated at 2-8°C (36-46°F)

Do not freeze or expose to high temperatures.

Protect from light.

See package insert for dosage and administration.

This Product Contains Dry Natural Rubber.

Rx only

Principal Display Panel - Carton Label

NDC 59627-333-04

Avonex Pen®
(interferon beta-1a)
Injection

30 mcg/0.5 mL Single-Use Prefilled Autoinjector

For Intramuscular Injection

Once a Week

Contents:

4 Avonex Pen® Administration Dose Packs

Store refrigerated at 2-8°C (36-46°F)

Do not freeze or expose to high temperatures. Protect from light.

The recommended dosage of Avonex® is 30 mcg injected intramuscularly
once weekly. See package insert for full prescribing information.

ATTENTION PHARMACIST: Each patient is required to receive the enclosed Medication Guide.

Principal Display Panel - Carton Label

NDC 59627-222-05

Avonex®
(interferon beta-1a)
Injection

30 mcg/0.5 mL Single-Use Prefilled Syringe

For Intramuscular Injection

Once a Week

Contents:

4 Avonex® Administration Dose Packs

ATTENTION PHARMACIST: Each patient is required to receive the enclosed Medication Guide.

This Product Contains Dry Natural Rubber.

Rx only

Store refrigerated at 2-8°C (36-46°F).

Do not freeze or expose to high temperatures.

Protect from light.

See package insert for dosage and administration.

Principal Display Panel - Tray Lid Label

Avonex® (interferon beta-1a)

30 mcg/0.5 mL Single-Use Prefilled Syringe

For Intramuscular Injection

Store refrigerated at 2-8°C (36-46°F). Do not freeze or expose to high temperatures.

Protect from light. Contents: 1 single-use prefilled syringe of Avonex® and 1, 23G, 1 1/4" needle. See package insert for dosage and administration. This Product Contains Dry Natural Rubber. ATTENTION PHARMACIST: Each patient is required to receive the enclosed Medication Guide. U.S. License# 1697

Biogen Inc., Cambridge, MA 02142 1-800-456-2255 Rx only 46043 -02

NDC 59627-002-07